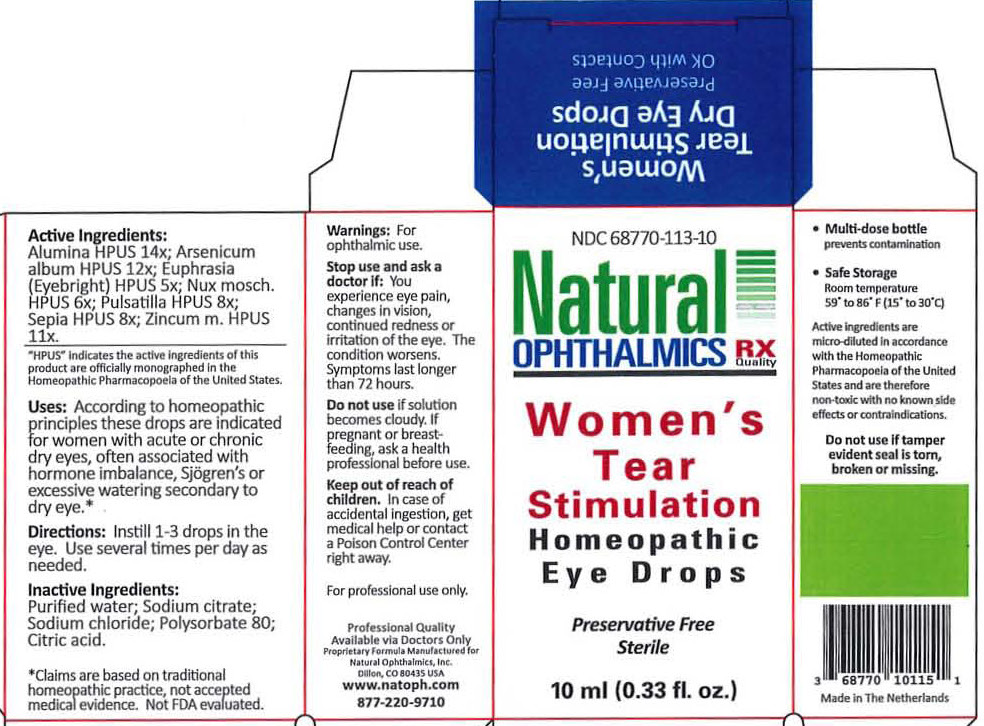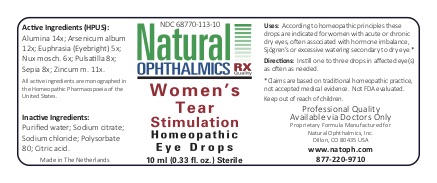 DRUG LABEL: Womens Tear Stimulation
NDC: 68770-113 | Form: LIQUID
Manufacturer: Natural Ophthalmics, Inc
Category: homeopathic | Type: HUMAN OTC DRUG LABEL
Date: 20220707

ACTIVE INGREDIENTS: PULSATILLA VULGARIS 8 [hp_X]/1 mL; SEPIA OFFICINALIS JUICE 8 [hp_X]/1 mL; EUPHRASIA STRICTA 5 [hp_X]/1 mL; ALUMINUM OXIDE 14 [hp_X]/1 mL; ARSENIC TRIOXIDE 12 [hp_X]/1 mL; NUTMEG 6 [hp_X]/1 mL; ZINC 11 [hp_X]/1 mL
INACTIVE INGREDIENTS: WATER; POLYSORBATE 80; CITRIC ACID MONOHYDRATE; SODIUM CHLORIDE

Women's Tear Stimulation

Homeopathic Purpose

- Pulsatilla 8x }
- Sepia 8x }
- Euphrasia (Eyebright) 5x }
- Alumina 10x } Dry eyes
- Arsenicum album 12x }
- Nux mosch 6x }
- Zincum met 10x }

Active Ingredients

Pulsatilla 8x
Sepia 8x
Euphrasia 5x
Alumina 10x
Arsenicum album 12x
Nux mosch 6x
Zincum m 11x

Inactive Ingredients

Purified water
Polysorbate 80
Sodium citrate
Sodium chloride

Uses

According to homeopathic principles these drops are indicated for Women with acute or chronic dry eyes, often associated with hormone imbalance, Sjogren's or excessive watering secondary to dry eye.

Directions

Instill 1-3 drops in the eye. Use several times per day as needed.

Warnings

For ophthalmic use.
For Professional Use Only

Keep out of reach of children. Incase of accidental ingestion, get medical help or contact a Poison Control Center right away.

Stop use and ask a doctor if: You experience eye pain, changes in vision, continued redness or irritation of the eye. The condition worsens. Symptoms last longer than 72 hours.

Do not use if solution becomes cloudy.

If pregnant or breast feeding, ask a health professional before use.

Storage

- Safe Storage

Room temperature
59o to 86o (15o to 30o C)

QUESTIONS

Natural Ophthalmics, Inc.
Lafayette, CO 80026 USA
www.natoph.com
877-220-9710